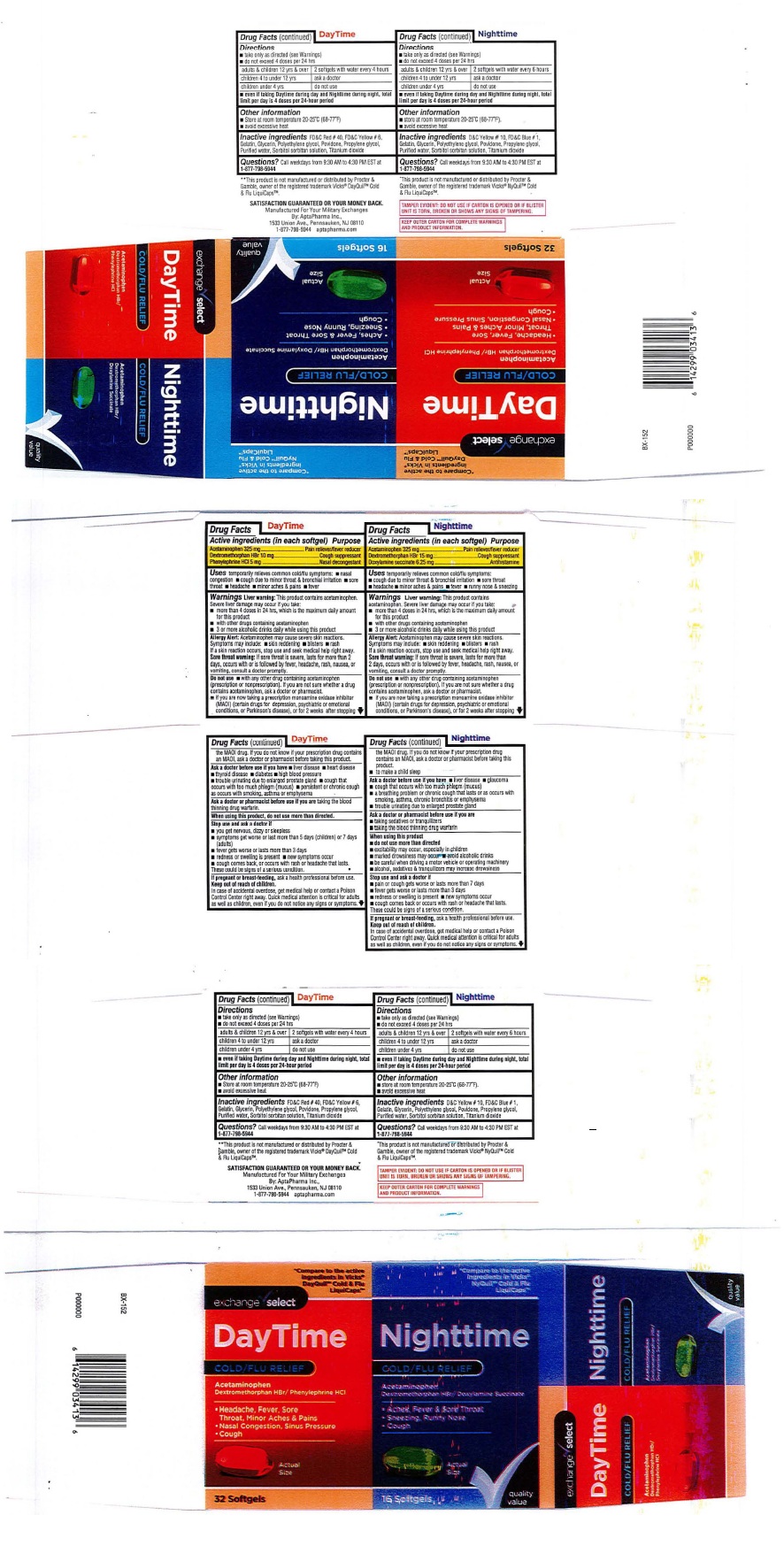 DRUG LABEL: DayTime and Nighttime Cold/Flu Relief Softgels - Combo Pack
NDC: 55301-605 | Form: KIT | Route: ORAL
Manufacturer: ARMY AND AIR FORCE EXCHANGE SERVICE
Category: otc | Type: HUMAN OTC DRUG LABEL
Date: 20251219

ACTIVE INGREDIENTS: ACETAMINOPHEN 325 mg/1 1; DEXTROMETHORPHAN HYDROBROMIDE 10 mg/1 1; PHENYLEPHRINE HYDROCHLORIDE 5 mg/1 1; ACETAMINOPHEN 325 mg/1 1; DEXTROMETHORPHAN HYDROBROMIDE 15 mg/1 1; DOXYLAMINE SUCCINATE 6.25 mg/1 1
INACTIVE INGREDIENTS: FD&C RED NO. 40; FD&C YELLOW NO. 6; GELATIN; GLYCERIN; POLYETHYLENE GLYCOL, UNSPECIFIED; POVIDONE; PROPYLENE GLYCOL; WATER; SORBITOL; SORBITAN; TITANIUM DIOXIDE; D&C YELLOW NO. 10; FD&C BLUE NO. 1; GELATIN; GLYCERIN; POLYETHYLENE GLYCOL, UNSPECIFIED; PROPYLENE GLYCOL; POVIDONE; WATER; SORBITOL; SORBITAN; TITANIUM DIOXIDE

exchange select DayTime and Nighttime Cold/Flu Relief Softgels - Combo Pack

------------

DayTime COLD/FLU RELIEF

Drug Facts

Active ingredients
(in each Softgel)

Acetaminophen ................325 mg

Dextromethorphan HBr ......10 mg

Phenylephrine HCl .........5 mg

Purpose

Acetaminophen ........................Pain reliever/Fever reducer

Dextromethorphan HBr .............Cough suppressant

Phenylephrine HCl ............... Nasal Decongestant

INDICATIONS AND USAGE

Usestemporarily relieves common cold/flu
symptoms: ■ nasal congestion ■cough due to
to minor throat & bronchial irritation ■ sore
throat ■ headache ■ minor aches and pains
■ fever

WARNINGS

WarningsLiver warning: This product
contains acetaminophen. Severe liver
damage may occur if you take ■ more than
4 doses in 24 hrs, which is the maximum
daily amount for this product ■ with other
drugs containing acetaminophen ■ 3 or more
alcoholic drinks daily while using this product.

Allergy Alert:Acetaminophen may cause
severe skin reactions. Symptoms may
include ■ skin reddening ■ blisters ■ rash.
If a skin reaction occurs, stop use and seek
medical help right away.

Sore throat warning:If sore throat is
severe, lasts for more than 2 days, occurs
with or is followed by fever, headache, rash,
nausea or vomiting, consult a doctor
promptly.

Do not use:

■ with any other products containing
acetaminophen (prescription or
nonprescription). If you are not sure whether
a drug contains acetaminophen, ask a doctor
or pharmacist.
■ if you are now taking a prescription
monoamine oxidase inhibitor (MAOI) (certain
drugs for depression, psychiatric, or
emotional conditions, or Parkinson's
disease), or for 2 weeks after stopping the
MAOI drug. If you do not know if your
prescription drug contains an MAOI, ask
a doctor or pharmacist before taking this
product.

Ask a doctor before use if you have
■ liver disease ■ heart disease
■ thyroid disease ■ diabetes
■ high blood pressure
■ trouble urinating due to enlarged prostate
gland
■ cough that occurs with too much phlegm
(mucus)
■ persistant or chronic cough as occurs with
smoking, asthma or emphysema

Ask a doctor or pharmacist before use if you aretaking the blood thinning drug warfarin.

When using this product, do not use more than directed.

Stop use and ask a doctor if

■ you get nervous, dizzy or sleepless
■ symptoms get worse or last more
than 5 days (children) or 7 days (adults)
■ fever gets worse or lasts more than 3 days
■ redness or swelling is present
■ new symptoms occur
■ cough comes back or occurs with rash or
headache that lasts.
These could be signs of a serious condition.

PREGNANCY OR BREAST FEEDING

If pregnant or breast-feeding,ask a health professional before use.

Keep out of reach of children.

OTHER SAFETY INFORMATION

In case of accidental overdose, get medical
help or contact a Poison Control Center right
away. Quick medical attention is critical for
adults as well as children, even if you do not
notice any signs or symptoms.

Directions
■ take only as directed (see Warnings)
■ do not exceed 4 doses per 24 hours

adults & children 12 yrs & over | 2 softgels with water every 4 hours
children 4 to under 12 yrs | ask a doctor
children under 4 yrs | do not use

■ even if taking DayTime during day and Nighttime during night, total
limit per day is 4 doses per 24-hour period.

Other information
■ Store at room temperature 20-25º C (68-77º F)
■ avoid excessive heat

INACTIVE INGREDIENT

Inactive ingredientsFD&C Red # 40, FD&C Yellow # 6,
Gelatin, Glycerin, Polyethylene glycol, Povidone, Propylene glycol,
Purified water, Sorbitol sorbitan solution, Titanium dioxide

QUESTIONS

Questions?Call Weekdays from 9:30 AM to 4:30 PM EST at
1-877-798-5944

------------

Nighttime COLD/FLU RELIEF

Drug Facts

Active ingredients
(in each Softgel)

Acetaminophen ................325 mg

Dextromethorphan HBr ......15 mg

Doxylamine succinate .........6.25 mg

Purpose

Acetaminophen ........................Pain reliever/fever reducer

Dextromethorphan HBr .............Cough suppressant

Doxylamine succinate ............... Antihistamine

INDICATIONS AND USAGE

Usestemporarily relieves common cold/flu
symptoms: ■ cough due to minor throat &
bronchial irritation ■ sore throat ■ headache
■ minor aches and pain ■ fever ■ runny
nose & sneezing

WARNINGS

WarningsLiver warning: This product
contains acetaminophen. Severe liver
damage may occur if you take ■ more than
4 doses in 24 hrs, which is the maximum
daily amount for this product ■ with other
drugs containing acetaminophen ■ 3 or more
alcoholic drinks daily while using this product.

Allergy Alert:Acetaminophen may cause
severe skin reactions. Symptoms may
include ■ skin reddening ■ blisters ■ rash.
If skin reaction occurs, stop use and seek
medical help right away.

Sore throat warning: If sore throat is
severe, lasts for more than 2 days, occurs
with or is followed by fever, headache, rash,
nausea or vomiting, consult a doctor
promptly.

Do not use:■ with any other products containing
acetaminophen (prescription or
nonprescription). If you are not sure whether
a drug contains acetaminophen, ask a doctor
or pharmacist.
■ if you are now taking a prescription
monoamine oxidase inhibitor (MAOI) (certain
drugs for depression, psychiatric, or
emotional conditions, or Parkinson's
disease), or for 2 weeks after stopping the
MAOI drug. If you do not know if your
prescription drug contains an MAOI, ask
a doctor or pharmacist before taking this
product.

■ to make a child sleep.

Ask a doctor before use if you have
■ liver disease ■ glaucoma
■ cough that occurs with too much phlegm
(mucus)
■ a breathing problem or chronic cough that
lasts or as occurs with smoking, asthma,
chronic bronchitis or emphysema
■ trouble urinating due to enlarged prostate
gland

Ask a doctor or pharmacist before use if you are
■ taking sedatives or tranquilizers
■ taking the blood thinning drug warfarin

When using this product

■ do not use more than directed
■ excitability may occur, especially in children
■ marked drowsiness may occur
■ avoid alcoholic drinks
■ be careful when driving a motor vehicle or
operating machinery
■ alcohol, sedatives & tranquilizers may
increase drowsiness

Stop use and ask a doctor if
■ pain or cough gets worse or lasts more
than 7 days
■ fever gets worse or lasts more than 3 days
■ redness or swelling
is present
■ new symptoms occur
■ cough comes back or occurs with rash or
headache that lasts.
These could be signs of a serious condition.

PREGNANCY OR BREAST FEEDING

If pregnant or breast-feeding, ask a health professional before use.

Keep out of reach of children.

OTHER SAFETY INFORMATION

In case of accidental overdose, get medical
help or contact a Poison Control center right
away. Quick medical attention is critical for
adults as well as children, even if you do not
notice any signs or symptoms.

Directions
■ take only as directed (see Warnings)
■ do not exceed 4 doses per 24 hours

adults & children 12 yrs & over | 2 softgels with water every 6 hours
children 4 to under 12 yrs | ask a doctor
children under 4 yrs | do not use

■ even if taking DayTime during day and Nighttime during night, total
l imit per day is 4 doses per 24-hour period.

Other information
■ Store at room temperature 20-25º C (68-77º F)
■ avoid excessive heat

Inactive ingredients
D&C Yellow # 10, FD&C
Blue # 1, Gelatin, Glycerin,
Polyethylene glycol,
Povidone, Propylene glycol,
Purified water, Sorbitol
sorbitan solution, Titanium
dioxide.

QUESTIONS

Questions? Call Weekdays from 9:30 AM to 4:30 PM EST at
1-877-798-5944

Principal Display Package Label: exchange select DayTime and Nighttime Cold/Flu Relief Softgels - Combo Pack

DayTime Cold/Flu Relief Nighttime Cold/Flu Relief

32 Softgels / 16 Softgels

**Compare to the active ingredients in **Compare to the active ingredients in
Vicks® DayQuil® Cold and Flu LiquiCaps® Vicks® NyQuil® Cold and Flu Liquicaps®

**This product is not manufactured or **This product is not manufactured or
distributed by Procter & Gamble, owner of distributed by Procter & Gamble, owner of
the registered trademark Vicks® DayQuil® � the registered trademark Vicks® NyQuil®
Cold & Flu LiquiCaps®. Cold & Flu LiquiCaps®.

TAMPER EVIDENT: DO NOT USE IF CARTON IS OPENED OR IF BLISTER
UNIT IS TORN, BROKEN OR SHOWS ANY SIGNS OF TAMPERING.

KEEP OUTER CARTON FOR COMPLETE WARNINGS
AND PRODUCT INFORMATION.

SATISFACTION GUARANTEED OR YOUR MONEY BACK.

Manufactured For Your Military Exchanges
By AptaPharma Inc.,
1533 Union Avenue, Pennsauken, NJ 08110
1-877-798-5944 aptapharma.com

res